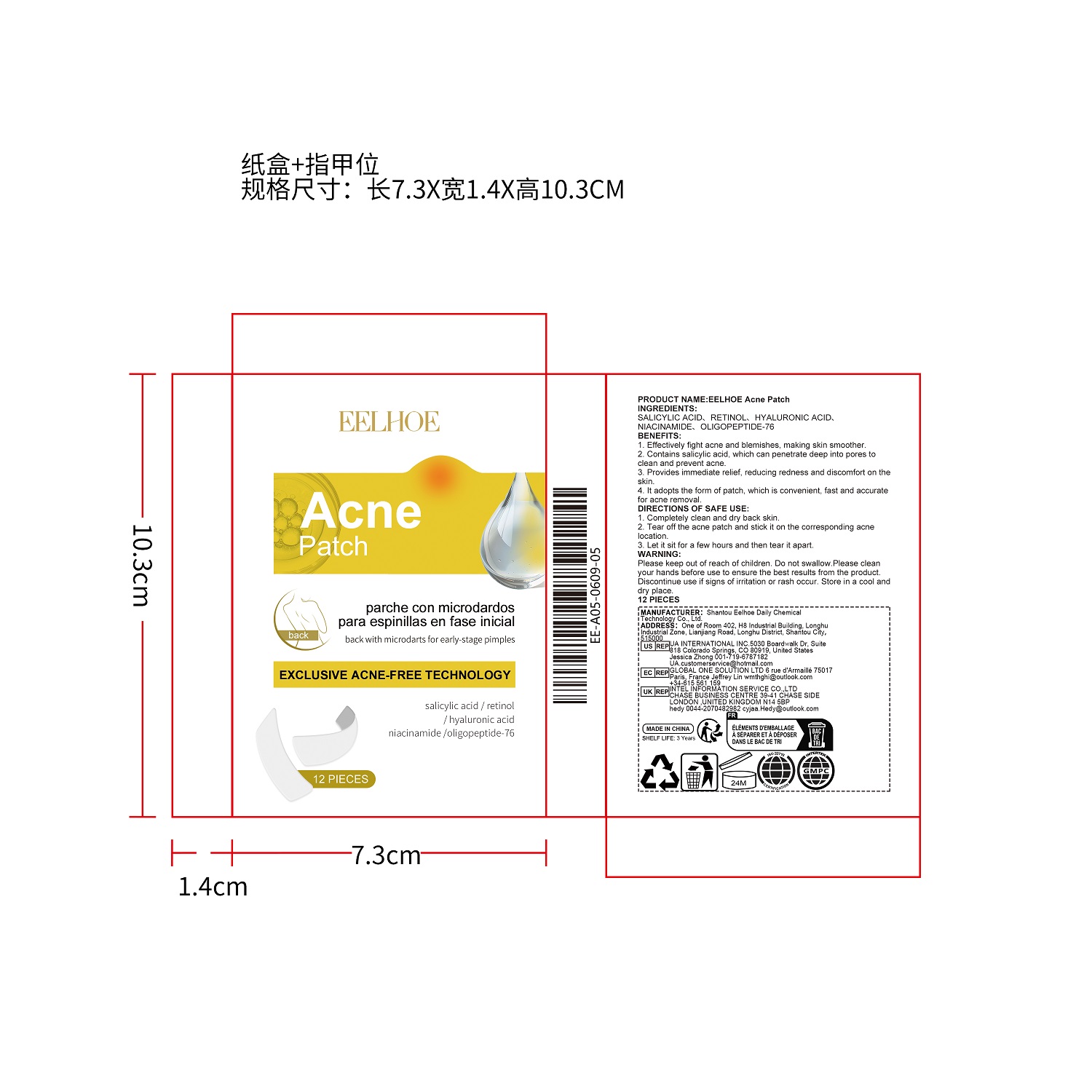 DRUG LABEL: EELHOE Acne
NDC: 85064-001 | Form: PATCH
Manufacturer: Shantou Eelhoe Daily Chemical Technology Co., Ltd.
Category: otc | Type: HUMAN OTC DRUG LABEL
Date: 20251127

ACTIVE INGREDIENTS: SALICYLIC ACID 0.02 g/100 g
INACTIVE INGREDIENTS: RETINOL; HYALURONIC ACID; NIACINAMIDE; OLIGOPEPTIDE-74

Active Ingredient(s)

SALICYLIC ACID

Purpose

1. Effectively fight acne and blemishes, making skin smoother.

2.Contains salicylic acid, which can penetrate deep into pores toclean and prevent acne.

3. Provides immediate relief, reducing redness and discomfort on theskin.

4. lt adopts the form of patch, which is convenient, fast and accuratefor acne removal.

none

Warnings

Please keep out of reach of children. Do not swallow.Please clean your hands before use toensure the best results from the product., Discontinue use if signs of irritation or rash occur. Storein a cool and dry place.

none

none

Please keep out of reach of children

STORAGE AND HANDLING

Store in a cool and dry place

INACTIVE INGREDIENT

RETINOL、HYALURONIC ACID、NIACINAMIDE、OLIGOPEPTIDE-76

DIRECTIONS OF SAFE USE:

1. Completely clean and dry back skin.

2. Tear off the acne patch and stick it on the corresponding acnelocation.

3. Let it sit for a few hours and then tear it apart.

INDICATIONS AND USAGE

NONE